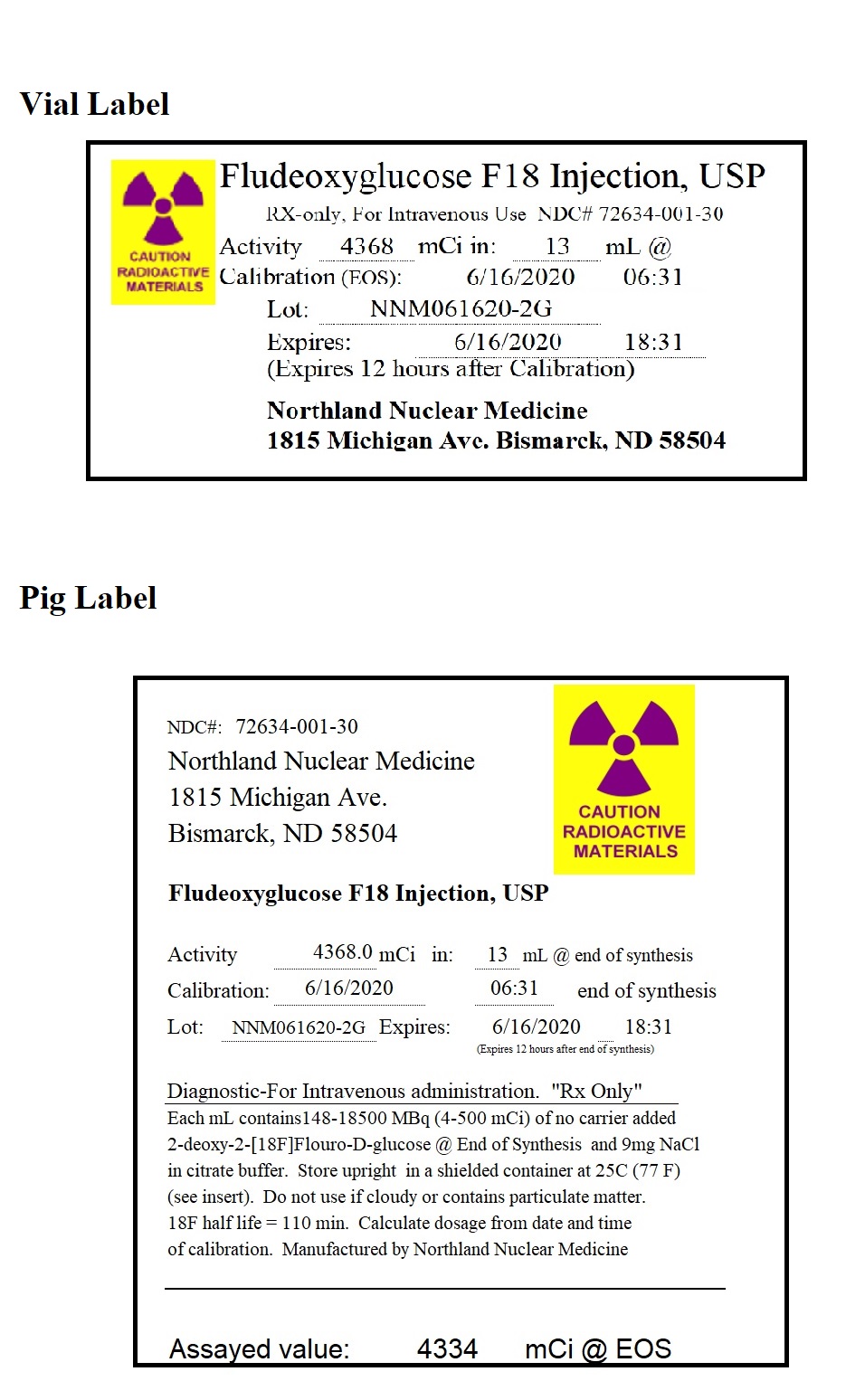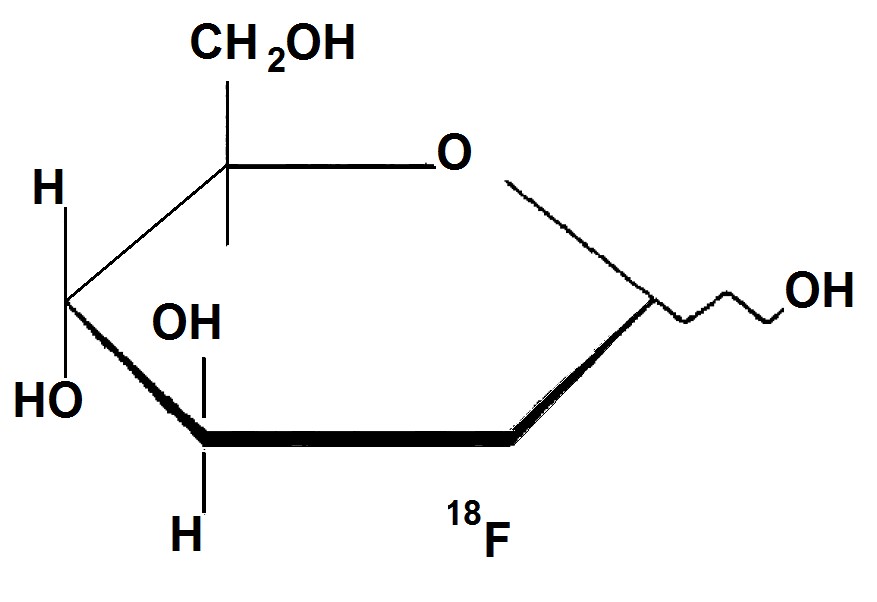 DRUG LABEL: Fludeoxyglucose F 18
NDC: 72634-001 | Form: INJECTION
Manufacturer: Northland Nuclear Medicine
Category: prescription | Type: HUMAN PRESCRIPTION DRUG LABEL
Date: 20200807

ACTIVE INGREDIENTS: FLUDEOXYGLUCOSE F-18 0.5 Ci/1 mL

30 ml Vial Label

DESCRIPTION

Fludeoxyglucose F18 Injection, USP is a positron emitting radiopharmaceutical containing no-carrier added radioactive 2-deoxy-2-[18F]fluoro-D-glucose that is used for diagnostic purposes in conjunction with Positron Emission Tomography (PET). It is administered by intravenous injection.

The active ingredient 2-deoxy-2-[18F]fluoro-D-glucose, abbreviated [18F]FDG, has a molecular formula of C8H1118F08 with a molecular weight of 181.26 daltons, and has the following chemical structure.

Fludeoxyglucose F18 Injection, USP is provided as a ready to use sterile, pyrogen free, clear, colorless solution. Each milliliter contain between 150 to 1850 MBq (4 — 500 mCi) of 2-deoxy-2-[18F]fluoro-D-glucose at the end of synthesis (EOS), and 9 mg of sodium chloride in citrate buffer. The pH of the solution is between 4.5 to 7.5. The solution is packaged in a multiple-dose glass vial and does not contain any preservative.

PHYSICAL CHARACTERISTICS

Fluorine F 18 decays by positron (+) emission and has a half life of 110 minutes. The principal photons useful for diagnostic imaging are the 511 keV gamma photons, resulting from the interaction of the emitted positron with an electron (Table 1)

Table 1. Principle Emission Data for Fluorine F-18
Radiation/Emission | % Per Disintigration | Mean Energy
Positron (+) | 96.73 | 249.8 keV
Gamma (+/-)* | 193.46 | 511.0 keV

*Produced by positron annihilation

From: Kocher, D.C. "Radioactive Dacay Tables" DOE/TIC-11026, 89 (1981).

EXTERNAL RADIATION

The specific gamma ray constant for Fluorine F 18 is 6.0 R/hr/mCi (0.3 Gy/hr/kBq) at 1cm. The half-value layer (HVL) for the 511 keV photons is 4.1 mm lead (Pb). A range of values for the attenuation of radiation results from the interposition of various thicknesses of Pb.

The range of attenuation coefficients for this radionuclide is shown in Table 2. For example the interposition of an 8.3 mm thickness of Pb, with a coefficient of attenuation of 0.25, will decrease the external radiation by 75%.

Table 2. Radiation Attenuation of 511 keV Photons by lead (Pb) Shielding
Shield Thickness (Pb) mm | Coefficient of Attenuation
0 | 0.00
4.1 | 0.50
8.3 | 0.25
13.2 | 0.10
26.4 | 0.01
52.8 | 0.001

For use in correcting for physical decay of this radionuclide, the fractions remaining at selected intervals after calibration are shown in table 3.

CLINICAL PHARMACOLOGY

General

[18F]FDG, a radiolabeled analog of glucose, rapidly distributes, after intravenous injection, to all organs of the body. After background clearance, peak imaging is at 30 - 40 minutes after injection.

Table 3. Physical Decay Chart for Fluorine F 18
Minutes | Fraction Remaining
0* | 1.00
15 | 0.909
30 | 0.826
60 | 0.683
110 | 0.500
220 | 0.250
440 | 0.060

*Calibration Time

Pharmacokinetics

In 4 normal male volunteers, after an intravenous dose given over 30 seconds, the arterial blood level profile for [18F]FDG can be described by a triexponential decay curve. The half-lives for the different distribution and elimination phases are 0.2-0.3 min, 10-13 min (mean ± s.d.; 11.6 ± 1.1 min), and 80-95 min (88 ± 4 min).

Within 33 minutes, a mean of 3.9% of the injected dose can be measured in the urine. Bladder activity two hours after injection indicates that a mean of 20.6% of the injected dose is present. See the Metabolism Section for additional clearance times.

Metabolism

[18F]FDG is taken up by cells and phosphorylated to [18F]FDG-6-phosphate at a rate proportional to the rate of glucose utilization within a given tissue. [18F]FDG-6-phosphate presumably is metabolized to 2- deoxy-2-[18F]fluoro-6-phospho-D-mannose ([18F]FDM-6-phosphate).

[18F]FDG may contain 2-deoxy-2-chloro-D-glucose (C1DG) as an impurity. Distribution and metabolism of C1DG are presumably similar to that of [18F]FDG, and would be expected to result in intracellular formation of 2-deoxy-2-chloro-6-phospho-D-g14icose (C1DG-6-phosphate) and 2-deoxy-2-chloro-6- phospho-D-mannose (CIDM-6-phosphate). The phosphorylated deoxyglucose compounds are dephosphorylated, and the resulting compounds, (FDG, FDM, C1DG and C1DM) presumably leave cells by passive diffusion.

FDG and related compounds are cleared from non-cardiac tissues within 3 to 24 hours after administration; clearance from the heart may require more than 96 hours. [18F]FDG that is not involved in glucose metabolism is excreted unchanged in the urine.

Pharmacodynamics

[18F]FDG is a glucose analogue which concentrates in cells that rely upon glucose as a primary energy source. Once in the cell it is phosphorylated and can not exit until dephosphorylation has occurred. Regions of “increased [18F]FDG uptake" correlate with increased glucose metabolism. Regions of decreased/absent uptake reflect the absence of glucose metabolism. Background activity reflects uptake by normal cells. [18F]FDG uptake in inflammatory cells is inconsistent and may be increased, normal or decreased. Whether or not [18F]FDG, CIDG, or their metabolites can inhibit glucose metabolism is not known.

CLINICAL TRIALS

In a prospective, open label trial, [18F]FDG was evaluated in 86 patients with epilepsy. Each patient received a dose of [18F]FDG in the range of 185-370 MBq (5-10) mCi. Demographic characteristics of race and gender are not available. The mean age was 16.4 years (range: 4 months - 58 years; of these, 42 patients were < 12 years and 16 patients were <2 years old). Patients had a known diagnosis of complex partial epilepsy and were under evaluation as surgical candidates for treatment of their seizure disorder. Seizure foci had been previously identified on ictal EEGs and sphenoidal EEGs. In 16% (14/87) of patients, the pre-[18F]FDG findings were confirmed by [18F]FDG; 34% (30/87) of patients, [18F]FDG scans provided new findings. In 32% (27/87), [18F]FDG scans were not definitive. The influence of these findings on surgical outcome; medical management or behavior is not known.

In several other studies comparing [18F]FDG scan results to subsphenoidal EEG, MRI and/or surgical findings, the degree of hypometabolism corresponded to areas of confirmed epileptogenic foci.

INDICATIONS AND USAGE

Fludeoxyglucose F 18 Injection,USP is indicated in PET (positron emission tomography) for:

1. Identification of regions of abnormal glucose metabolism associated with foci of epileptic seizures.

2. Assessment of abnormal glucose metabolism to assist in the evaluation of malignancy in patients with known or suspected abnormalities found by other testing modalities, or in patients with an existing diagnosis of cancer.

3. Assessment of patients with coronary artery disease and left ventricular dysfunction, when used together with myocardial perfusion imaging, for the identification of left ventricular myocardium with residual glucose metabolism and reversible loss of systolic function.

Fludeoxyglucose F 18 Injection, USP is not indicated for distinguishing epileptogenic foci from brain tumors or other brain lesions which may cause seizures.

WARNINGS

None known

CONTRAINDICATIONS

None known

PRECAUTIONS

General

[18F]FDG uptake may be changed by fasting or by blood sugar changes associated with diabetic mellitus. Blood glucose levels should be stabilized in non-diabetic patients by fasting before [18F]FDG injection. Diabetic patients may need stabilization of blood glucose on the day preceding, and on the day of the [18F]FDG scan.

Patients should be monitored for arrhythmias and other manifestations of ischemia. [18F]FDG, CIDG and their metabolites theoretically could inhibit glucose metabolism. Their ability to potentiate the arrhythmogenic effects of ischemia has not been studied.

The contents of each vial are sterile and non-pyrogenic. To maintain sterility, aseptic technique must be used during all operations involved in the manipulation and administration of [18F]FDG.

[18F]FDG should be used within 12 hours of the end of synthesis (EOS).

As with any other radioactive material, appropriate shielding should be used to avoid unnecessary radiation exposure to the patient, occupational workers, and other persons.

Radiopharmaceuticals should be used only by physicians who are qualified by specific training in the safe use and handling of radionuclides.

Carcinogenesis, Mutagenesis, Impairment of Fertility

Studies with [18F]FDG have not been performed to evaluate carcinogenic potential, mutagenic potential or effects on fertility.

Teratogenic Effects: Pregnancy Category C

Animal reproduction studies have not been conducted with [18F]FDG. It is not known whether [18F]FDG can cause fetal harm when administered to a pregnant woman or can affect reproduction capacity. Therefore, [18F]FDG should not be administered to a pregnant woman unless the potential benefit justifies the potential risk to the fetus.

Nursing Mothers

It is not known whether this drug is excreted in human milk. Because many drugs are excreted in human milk, caution should be exercised when [18F]FDG is administered to a nursing woman.

Pediatric Use

See Clinical Trials Section.

ADVERSE REACTIONS

The [18F]FDG safety data base was evaluated for 374 patients. Of these, 245 were male and 105 were female. For 24 patients, gender was not specified. The mean age was 47.8 years (range under 2 to over 65 years). Eighteen patients were between the age of 0 and 2 years; 42 patients were between the ages of 2 and 21 years old; 213 patients were between 21 and 65 years old and 98 patients were older than 65 years and the ages of 3 male patients were not specified. A racial distribution is not available. In this database, adverse drug reactions that required medical intervention were not reported.

In a small, 42 patient subset of the 374 patients studied, 4 patients had transient hypotension, 6 had hypo- or hyperglycemia and 3 had transient increases in alkaline phosphatase.

DOSAGE AND ADMINISTRATION

[18F]FDG uptake may be changed by fasting or by blood sugar changes associated with diabetic mellitus. Blood glucose levels should be stabilized in non-diabetic patients by fasting before [18F]FDG injection. Diabetic patients may need stabilization of blood glucose on the day preceding and on the day of the [18F]FDG scan.

The recommended dose of [18F]FDG for an adult (70 kg) is within the range 185-370 MBq (5-10 mCi), intravenous injection. In children doses as low as 2.6 mCi have been given. Optimal dose reductions for children have not been confirmed.

The optimum rate of administration and upper safe dose for [18F]FDG have not been established. The time interval between doses of [18F]FDG should be long enough to allow substantial decay (physical and biological) of previous administrations.

It is recommended that PET imaging be initiated within 40 minutes of [18F]FDG injection.

The final dose for the patient should be calculated using proper decay factors from the time of the EOS, and measured by a suitable radioactivity calibration system before administration. See decay factors in Table 3.

[18F]FDG, like other parenteral drug products, should be inspected visually for particulate matter and discoloration before administration, whenever solution and container permit. Preparations containing particulate matter or discoloration should not be administered. They should be disposed of in a safe manner, in compliance with applicable regulations.

[18F]FDG should be stored upright in a lead shielded environment at controlled room temperature.

Aseptic techniques and effective shielding should be employed in withdrawing doses for administration to patients. Waterproof gloves and effective shielding should be worn when handling the product.

OVERDOSE

Overdoses of [18F]FDG have not been-reported. See Radiation Dosimetry Section for related information.

RADIATION DOSIMETRY

The estimated absorbed radiation doses to an average human adult (70 kg) from intravenous injection of 185 MBq (5 mCi) and 370 MBq (10 mCi) of [18F]FDG are shown is Table 4. These estimates were calculated based on human1 data and using the data published by the International Commission on Radiological Protection2 for [18F]FDG.

Table 4. Estimated Absorbed Radiation Doses after intravenous administration of 2-deoxy-2-[18F]fluoro-D-glucose, [18F]FDG to a 70 kg patient.
Organ | MgY/185MBq | Rads/5mCi | mGy/370MBq | rads/10mCi
Bladder Wall | 31.45 | 3.15 | 62.90 | 6.29
Bladder* | 11.00 | 1.10 | 22.00 | 2.20
Bladder** | 22.00 | 2.20 | 44.00 | 4.40
Heart | 12.03 | 1.20 | 24.05 | 2.41
Brain | 4.81 | .48 | 9.62 | 0.96
Kidneys | 3.88 | 0.39 | 7.77 | 0.78
Uterus | 3.70 | 3.7 | 7.40 | 0.74
Ovaries | 2.78 | 0.28 | 5.55 | 0.56
Testes | 2.78 | 0.28 | 5.55 | 0.56
Adrenals | 2.59 | 0.26 | 5.18 | 0.52
Sm Intestine | 2.40 | 0.24 | 4.81 | 0.48
ULI wall | 2.40 | 0.24 | 4.81 | 0.48
LLI wall | 2.96 | 0.30 | 5.92 | 0.59
Stomach wall | 2.22 | 0.22 | 4.44 | 0.44
Liver | 2.22 | 0.22 | 4.44 | 0.44
Pancreas | 2.22 | 0.22 | 4.44 | 0.44
Spleen | 2.22 | 0.22 | 4.44 | 0.44
Breast | 2.04 | 0.20 | 4.07 | 0.41
Lungs | 2.04 | 0.20 | 4.07 | 0.41
Red marrow | 2.04 | 0.20 | 4.07 | 0.41
Other Tissue | 2.04 | 0.20 | 4.07 | 0.41
Bone Surfaces | 1.85 | 0.18 | 3.70 | 0.37
Thyroid | 1.70 | 0.18 | 3.59 | 0.36

*With void 1 hour after administration **With void 2 hours after administration.

The [18F]FDG Effective dose equivalent (Adult)2 is 0.027 mSv/MBq.

^1Jones, S.C. , Alavi, A., Christman, D., Montanez, I., Wolf, A.P., and Reivich, M. (1982). The Radiation Dosimetry of 2-F-18 fluoro-2-deoxy-D-glucose in man. J. Nucl. Med. 23, 613-617.

^2ICRP Publication 53, Volume 18, No. 1-4, 1987, page 76.

HOW SUPPLIED

NDC 72634-001-30

Fludeoxyglucose F18 Injection, USP is supplied in a multi-dose, septum capped 30 mL glass vial containing between 148 - 1480 MBq/mL (4 — 500 mCi/mL) of no carrier added 2-deoxy-2-[18F]fluoro-D-glucose at end of synthesis, in approximately 13 mL.

This radiopharmaceutical is licensed by the North Dakota Department of Health for distribution to persons authorized to receive the licensed material pursuant to the terms and conditions of a specific license issued by the U.S. Nuclear Regulatory Commission or an Agreement State.

Storage

[18F]FDG should be stored upright in a lead shielded container at controlled room temperature.

Storage and disposal of [18F]FDG should be in accordance with the regulations and a specific license issued by the U.S. Nuclear Regulatory Commission or an Agreement State.

Expiration Date and Time

Fludeoxyglucose F18 Injection, USP should be used within 12 hours from the end of synthesis, which is provided on the container label.

Caution: Federal Law Prohibits Dispensing Without Prescription

Manufactured by:

Northland Nuclear Medicine

1815 Michigan Ave

Bismarck, ND 58504